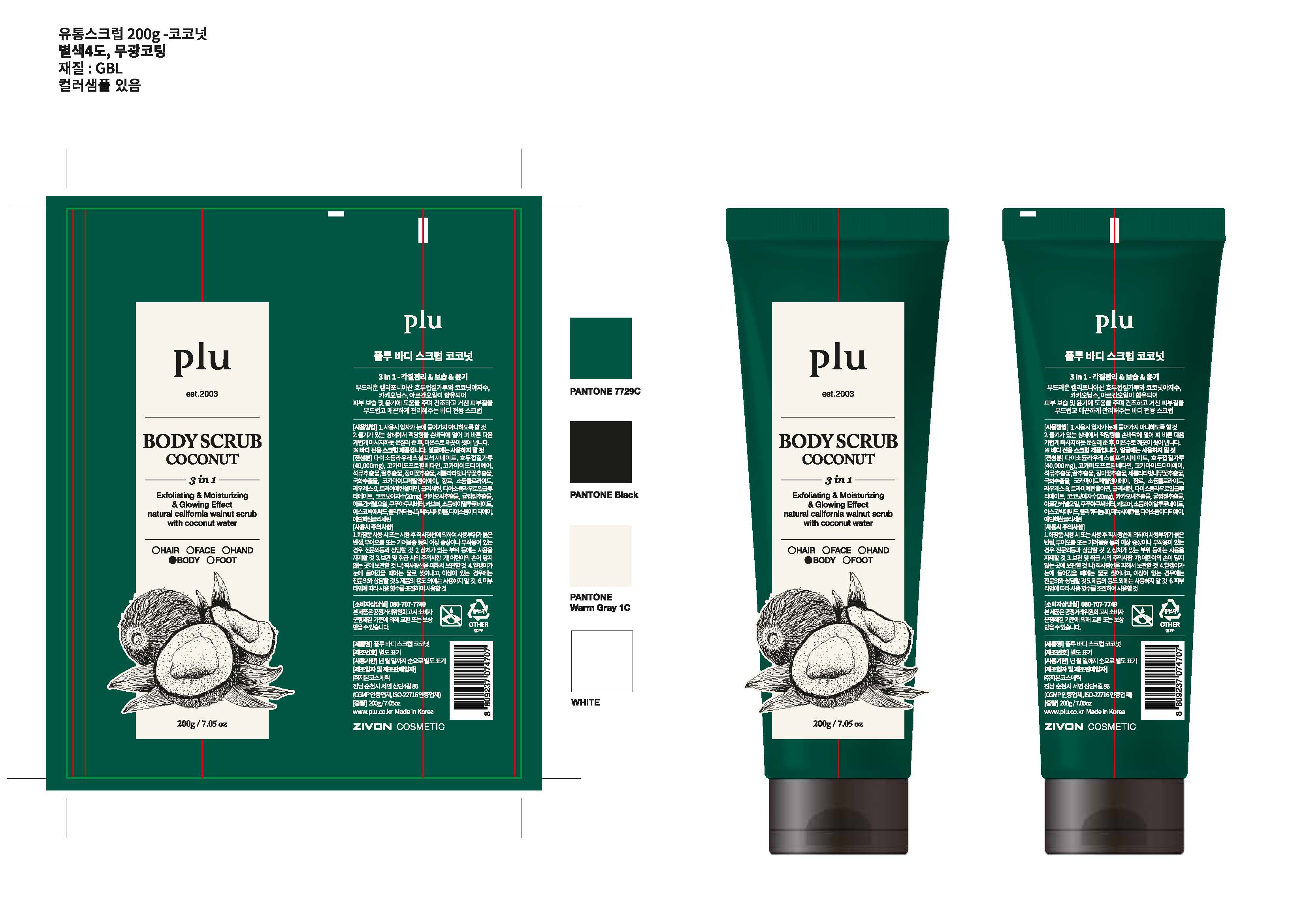 DRUG LABEL: Plu Body Scrub Coconut
NDC: 71503-004 | Form: LOTION
Manufacturer: Zivon Cosmetic Co., Ltd.
Category: otc | Type: HUMAN OTC DRUG LABEL
Date: 20190116

ACTIVE INGREDIENTS: Glycerin 3.38 g/200 mL
INACTIVE INGREDIENTS: Disodium Laureth Sulfosuccinate; Cocamidopropyl Betaine; Sodium Chloride; Disodium Lauroyl Glutamate; Theobroma Grandiflorum Seed Butter; Ascorbic Acid; Ethylhexylglycerin

ACTIVE INGREDIENT

Glycerin (1.69%) - Skin Protectant

INACTIVE INGREDIENT

Disodium Laureth Sulfosuccinate, Juglans Regia (Walnut) Shell Powder, Cocamidopropyl Betaine, Cocamide DEA, Cocamide Methyl MEA, Punica Granatum Fruit Extract, Honey Extract, Rosa Hybrid Flower Extract, Prunus Serrulata Flower Extract, Chrysanthemum Morifolium Flower Extract, Fragrance, Sodium Chloride, Laureth-9, Triethanolamine, Disodium Lauroyl Glutamate, Cocos Nucifera (Coconut) Water, Theobroma Cacao (Cocoa) Seed Extract, Citrus Unshiu Peel Extract, Argania Spinosa Kernel Oil, Theobroma Grandiflorum Seed Butter, Carbomer, Sodium Hyaluronate, Ascorbic Acid, Polyquaternium-10, Phenoxyethanol, Disodium EDTA, Ethylhexylglycerin

PURPOSE

Skin Protectant

WARNINGS

The safety of this product has not been determined.
1. Stop using of this product if any below symptom is found. Continuous use may worsen the symptom. Please contact dermatologist. a. In case of any troubles, such as red spots, swollen skin, itchy or irritation. b. In case of any trouble on applied area as above due to direct light.
2. Do not apply on trouble area such as wound, eczema or dermatitis.
3. Cautions for storage and handling a. After use, make sure to close cap. b. Keep away from reach of children. c. Do not keep in area where temperature is too hight or too low and avoid direct light.
4. Do not use other than product's specified application.
5. In case of use for baby or children, be careful not to rub eyes or put into mouth.
6. Excessive rubbing may cause wound.
7. Adjust application frequency by type of skin.
8. This is a scrub product especially for body. Do not apply to face
9. In use, be careful not have scrub particles get into eyes.
10. When particle gets into eyes, do not rub but wash out with water. If particle resides in eyes, please consult with medical doctor.

KEEP OUT OF REACH OF CHILDREN

If swallowed, get medical help or contact a Poison Control Center right away

INDICATIONS & USAGE

Wet Skin. Apply scrub on face and gently massage except eye area and rinse thoroughly with lukewarm water. *Do not use on face.

DOSAGE & ADMINISTRATION

Wet Skin. Apply scrub on face and gently massage except eye area and rinse thoroughly with lukewarm water. Do not use on face.